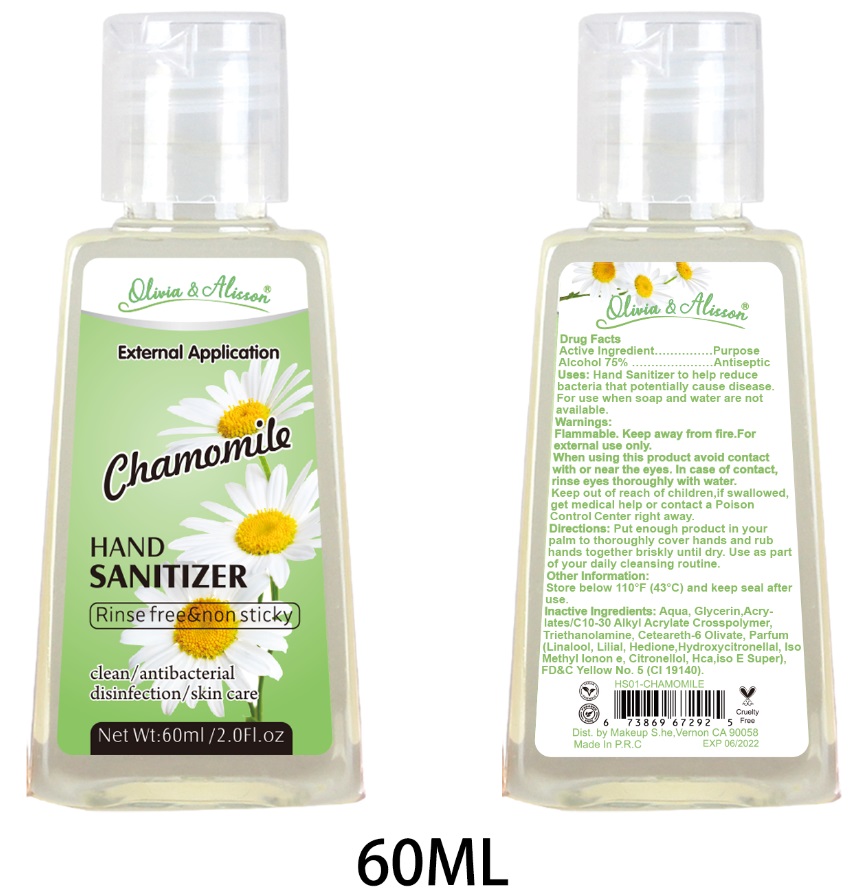 DRUG LABEL: HAND SANITIZER
NDC: 54823-005 | Form: GEL
Manufacturer: FUJIAN ISHINE COSMETICS CO., LTD.
Category: otc | Type: HUMAN OTC DRUG LABEL
Date: 20200506

ACTIVE INGREDIENTS: ALCOHOL 75 mL/100 mL
INACTIVE INGREDIENTS: .ALPHA.-HEXYLCINNAMALDEHYDE 0.01 mL/100 mL; CETEARETH-6 OLIVATE 0.1 mL/100 mL; LINALOOL, (+/-)- 0.01 mL/100 mL; METHYL DIHYDROJASMONATE (SYNTHETIC) 0.01 mL/100 mL; HYDROXYCITRONELLAL 0.01 mL/100 mL; ISOMETHYL-.ALPHA.-IONONE 0.01 mL/100 mL; FD&C YELLOW NO. 5 0.0001 mL/100 mL; TROLAMINE 0.3 mL/100 mL; BUTYLPHENYL METHYLPROPIONAL 0.01 mL/100 mL; .BETA.-CITRONELLOL, (+/-)- 0.01 mL/100 mL; 1-(2,3,8,8-TETRAMETHYL-1,2,3,4,5,6,7,8-OCTAHYDRONAPHTHALEN-2-YL)ETHANONE 0.01 mL/100 mL; WATER 23.9899 mL/100 mL; GLYCERIN 0.3 mL/100 mL; CARBOMER INTERPOLYMER TYPE A (55000 CPS) 0.3 mL/100 mL

HAND SANITIZER

Active Ingredient

ALCOHOL 75%

Purpose

Antiseptic

Uses:

Hand Sanitizer to help reduce bacteria that potentially cause disease. For use when soap and water are not available.

Warnings

Flammable. Keep away from fire.For external use only.

When using this product avoid contact with or near the eyes. In case of contact,rinse eyes thoroughly with water.

Keep out of reach of children,if swallowed, get medical help or contact a Poison Control Center right away.

Directions:

Put enough product in your palm to thoroughly cover hands and rub hands together briskly until dry. Use as part of your daily cleansing routine.

Other Information

Store below 110°F (43°C) and keep seal after use.

Inactive Ingredients:

Aqua, Glycerin, Acrylates/C10-30 Alkyl Acrylate Crosspolymer, Triethanolamine, Ceteareth-6 Olivate, Parfum (Linalool, Lilial, Hedione, Hydroxycitronellal, Iso Methyl Ionon e, Citronellol, iso E Super), FD&C Yellow No.5 (CI 19140).

Package Label

External Application

Chamomile

HAND SANITIZER

Rinse free&non sticky

Clean/antibacterial

Disinfection/skin care

Net Wt:60ml / 2.0fl.oz

NDC: 54823-005-01